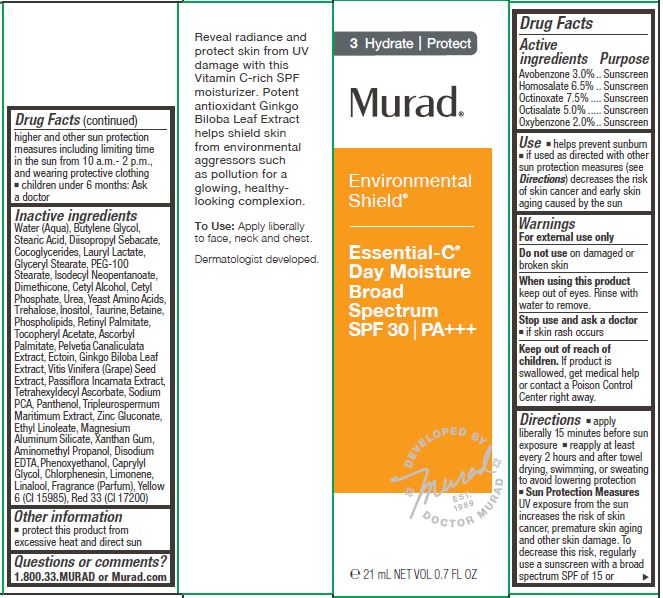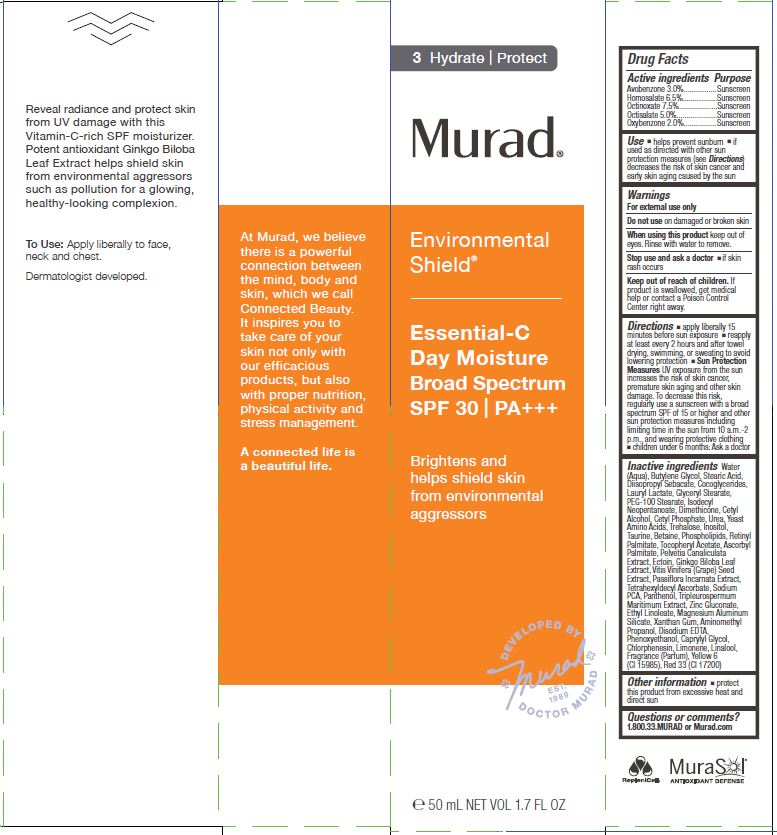 DRUG LABEL: MURAD - ENVIRONMENTAL SHIELD - ESSENTIAL-C DAY MOISTURE BROAD SPECTRUM 
NDC: 70381-103 | Form: LOTION
Manufacturer: Murad, LLC
Category: otc | Type: HUMAN OTC DRUG LABEL
Date: 20210129

ACTIVE INGREDIENTS: AVOBENZONE 3 g/100 mL; HOMOSALATE 10 g/100 mL; OCTINOXATE 7.5 g/100 mL; OCTISALATE 5 g/100 mL; OXYBENZONE 2 g/100 mL
INACTIVE INGREDIENTS: WATER; BUTYLENE GLYCOL; STEARIC ACID; DIISOPROPYL SEBACATE; COCO-GLYCERIDES; LAURYL LACTATE; GLYCERYL MONOSTEARATE; PEG-100 STEARATE; ISODECYL NEOPENTANOATE; DIMETHICONE; CETYL ALCOHOL; CETYL PHOSPHATE; UREA; AMINO ACIDS, SOURCE UNSPECIFIED; TREHALOSE; INOSITOL; TAURINE; BETAINE; OMEGA-3 FATTY ACIDS; VITAMIN A PALMITATE; .ALPHA.-TOCOPHEROL ACETATE; ASCORBYL PALMITATE; PELVETIA CANALICULATA; ECTOINE; GINKGO BILOBA WHOLE; VITIS VINIFERA SEED; PASSIFLORA INCARNATA WHOLE; TETRAHEXYLDECYL ASCORBATE; SODIUM PYRROLIDONE CARBOXYLATE; PANTHENOL; TRIPLEUROSPERMUM INODORUM WHOLE; ZINC GLUCONATE; ETHYL LINOLEATE; MAGNESIUM ALUMINUM SILICATE; XANTHAN GUM; AMINOMETHYLPROPANOL; EDETATE DISODIUM; PHENOXYETHANOL; CAPRYLYL GLYCOL; CHLORPHENESIN; LIMONENE, (+)-; LINALOOL, (+)-; FD&C YELLOW NO. 6; D&C RED NO. 33

MURAD - ENVIRONMENTAL SHIELD - ESSENTIAL-C DAY MOISTURE BROAD SPECTRUM SPF30

ACTIVE INGREDIENTS

Avobenzone 3.0%
Homosalate 6.5%
Octinoxate 7.5%
Octisalate 5.0%
Oxybenzone 2.0%

PURPOSE

SUNSCREEN

USES

- helps prevent sunburn
- if used as directed with other sun protection measures (see Directions) decreases the risk of skin cancer and early skin aging caused by the sun.

WARNINGS

For external use only
Do not use on damaged or broken skin
When using this product keep out of eyes. Rinse with water to remove.
Stop use and ask a doctor

- if rash occurs

Keep out of reach of children. If product is swallowed, get medical help or contact a Poison Control Center right away.

DIRECTIONS

- apply liberally 15 minutes before sun exposure
- use a water resistant sunscreen if swimming or sweating
- reapply at least every 2 hours
- Sun Protection Measures.pending time in the sun increases your risk of skin cancer and early skin aging. To decrease this risk, regularly use a sunscreen with a Broad Spectrum SPF value of 15 or higher and other sun protection measures including:
- limit time in the sun, especially from 10 a.m. - 2 p.m.
- wear long-sleeved shirts, pants, hats, and sunglasses.
- children under 6 months of age: ask a doctor

INACTIVE INGREDIENTS

Water (Aqua), Butylene Glycol, Stearic Acid, Diisopropyl Sebacate, Cocoglycerides, Lauryl Lactate, Glyceryl Stearate, PEG-100 Stearate, Isodecyl Neopentanoate, Dimethicone, Cetyl Alcohol, Cetyl Phosphate, Urea, Yeast Amino Acids, Trehalose, Inositol, Taurine, Betaine, Phospholipids, Retinyl Palmitate, Tocopheryl Acetate, Ascorbyl Palmitate, Pelvetia Canaliculata Extract, Ectoin, Ginkgo Biloba Leaf Extract, Vitis Vinifera (Grape) Seed Extract, Passiflora Incarnata Extract, Tetrahexyldecyl Ascorbate, Sodium PCA, Panthenol, Tripleurospermum Maritimum Extract, Zinc Gluconate, Ethyl Linoleate, Magnesium Aluminum Silicate, Xanthan Gum, Aminomethyl Propanol, Disodium EDTA, Phenoxyethanol, Caprylyl Glycol, Chlorphenesin, Limonene, Linalool, Fragrance (Parfum), Yellow 6 (CI 15985), Red 33 (CI 17200)

OTHER INFORMATION

- protect this product from excessive heat and direct sun

QUESTIONS OR COMMENTS?

1.800.33.MURAD or Murad.com